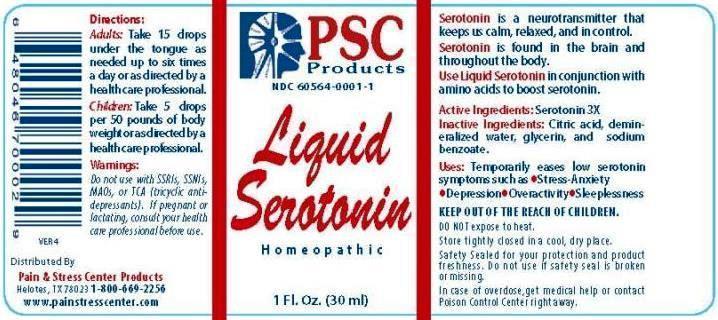 DRUG LABEL: Liquid Serotonin
NDC: 60564-0001 | Form: LIQUID
Manufacturer: Pain and Stress Center Products
Category: homeopathic | Type: HUMAN OTC DRUG LABEL
Date: 20240110

ACTIVE INGREDIENTS: SEROTONIN HYDROCHLORIDE 3 [hp_X]/1 mL
INACTIVE INGREDIENTS: CITRIC ACID MONOHYDRATE; WATER; GLYCERIN; SODIUM BENZOATE

DRUG FACTS:

ACTIVE INGREDIENTS:

Serotonin 3X

USES:

Temporarily eases low serotonin symptoms such as - Stress-Anxiety - Depression - Overactivity - Sleeplessness

Serotonin is a neurotransmitter that keeps us calm, relaxed, and in control. Serotonin is found in the brain and throughout the body. Use Liquid Serotonin in conjunction with amino acids to boost serotonin.

DIRECTIONS:

Adults: Take 15 drops under the tounge as needed up to six times a day or as directed by a health care professional.

Children: Take 5 drops per pounds of body weight or as directed by a health care professional.

INACTIVE INGREDIENTS:

Citric acid, demineralized water, glycerin, and sodium benzoate.

KEEP OUT OF THE REACH OF CHILDREN:

In case of overdose, get medical help or contact a Posion Control Center right away.

USES:

Temporarily eases low serotonin symptoms such as - Stress-Anxiety - Depression - Overactivity - Sleeplessness

Serotonin is a neurotransmitter that keeps us calm, relaxed, and in control. Serotonin is found in the brain and throughout the body. Use Liquid Serotonin in conjunction with amino acids to boost serotonin.

QUESTIONS:

Distributed By

Pain and Stress Center Products
Helotes, TX 78023 1-800-669-2256

www.painstresscenter.com

Package Label Display

PSC

Products

NDC 60564-0001-1

Liquid

Serotonin

Homeopathic

1 FL. Oz. (30 ml)